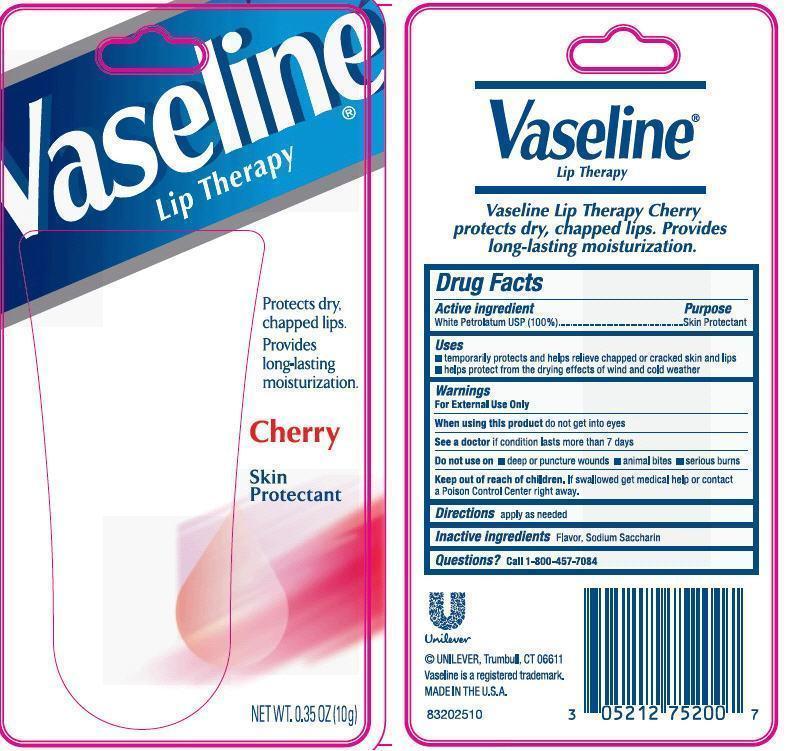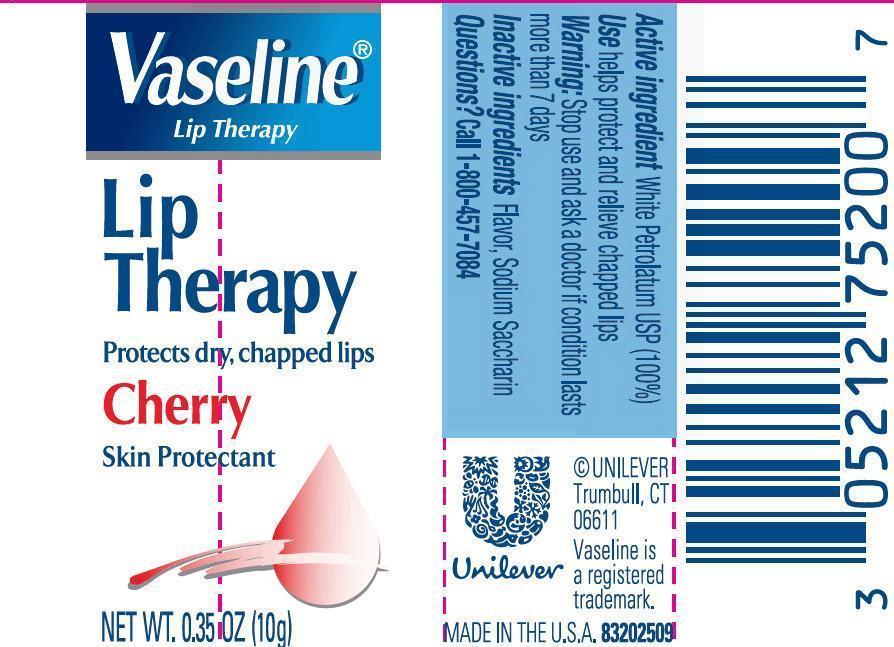 DRUG LABEL: Vaseline
NDC: 64942-0054 | Form: OINTMENT
Manufacturer: Conopco Inc. d/b/a Unilever
Category: otc | Type: HUMAN OTC DRUG LABEL
Date: 20121002

ACTIVE INGREDIENTS: petrolatum 100 g/100 g
INACTIVE INGREDIENTS: SACCHARIN SODIUM DIHYDRATE

Vaseline Lip Therapy Cherry

Active ingredient
WHITE PETROLATUM, USP (100%)

Purpose:
Skin Protectant

Uses
▪ temporarily protects and helps relieve chapped or cracked skin and lips
▪ helps protect from the drying effects of wind and cold weather

Warnings
For External Use Only

When using this product do not get in eyes

ASK DOCTOR

See a doctor if condition lasts more than 7 days

Do not use on ▪deep or puncture wounds ▪animal bites ▪serious burns

Keep out of reach of children. If swallowed get medical help or contact a Poison Control Center right away.

DOSAGE AND ADMINISTRATION

Directions apply as needed

Inactive Ingredient Flavor, Sodium Saccharin

Questions? Call 1-800-457-7084

PACKAGE LABEL

VLT Cherry 0.35 oz. PDP

PACKAGE LABEL

VLT Cherry Blister Card